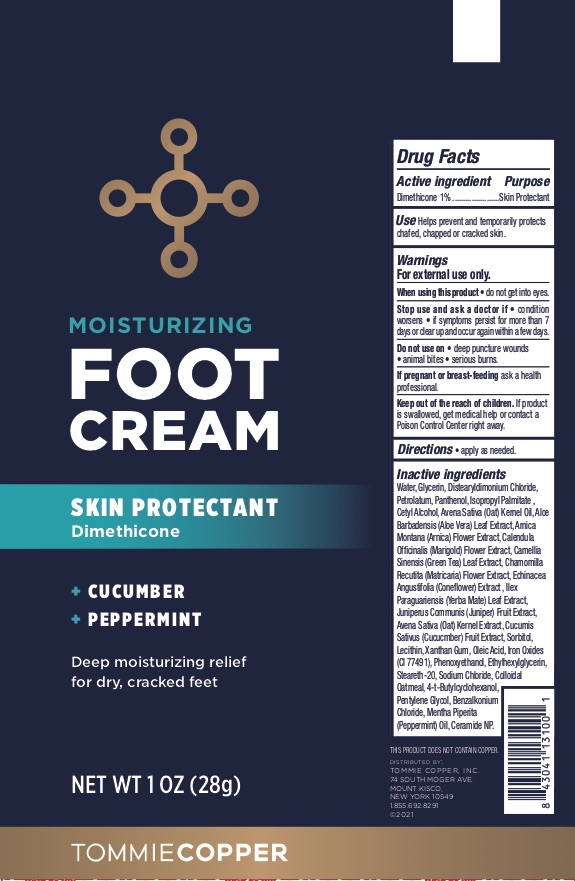 DRUG LABEL: Tommie Copper Foot
NDC: 72562-222 | Form: CREAM
Manufacturer: Tommie Copper, Inc.
Category: otc | Type: HUMAN OTC DRUG LABEL
Date: 20241215

ACTIVE INGREDIENTS: DIMETHICONE 1 g/100 g
INACTIVE INGREDIENTS: LECITHIN, SOYBEAN; XANTHAN GUM; OATMEAL; BENZALKONIUM CHLORIDE; 4-TERT-BUTYLCYCLOHEXANOL; PENTYLENE GLYCOL; ETHYLHEXYLGLYCERIN; CERAMIDE NP; STEARETH-20; PETROLATUM; CHAMOMILE; GREEN TEA LEAF; CUCUMBER; FERRIC OXIDE RED; CALENDULA OFFICINALIS FLOWER; WATER; OLEIC ACID; STEARIC ACID; GLYCERIN; ALOE VERA LEAF; ECHINACEA ANGUSTIFOLIA LEAF; ILEX PARAGUARIENSIS LEAF; CETYL ALCOHOL; ARNICA MONTANA FLOWER; JUNIPER BERRY; PEPPERMINT OIL; PHENOXYETHANOL; SODIUM CHLORIDE; ISOPROPYL PALMITATE; OAT KERNEL OIL; OAT; SORBITOL; PANTHENOL; DISTEARYLDIMONIUM CHLORIDE

TC Foot Cream

ACTIVE INGREDIENT

Dimethicone 1%

PURPOSE

Skin Protectant

INDICATIONS AND USAGE

Helps prevent and temporarily protects chafed, chapped, or cracked skin.

WARNINGS

For external use only. When using this product do not get into eyes. Stop use and ask a doctor if condition worsens, if symptoms persist for more than 7 days or clear up and occur again within a few days. Do not use on deep puncture wounds, animal bites, and serious burns.

PREGNANCY OR BREAST FEEDING

If pregnant or breast-feeding ask a health professional.

KEEP OUT OF REACH OF CHILDREN

If swallowed, get medical help or contact a Poison Control Center right away.

DOSAGE AND ADMINISTRATION

Apply as needed.

INACTIVE INGREDIENT

Water, Glycerin, Distearyldimonium Chloride, Petrolatum, Panthenol, Isopropyl Palmitate, Cetyl Alcohol, Avena Sativa (Oat) Kernel Oil, Aloe Barbadensis (Aloe Vera) Leaf Extract, Arnica Montana (Arnica) Flower Extract, Calendula Officinalis (Marigold) Flower Extract, Camellia Sinensis (Green Tea) Leaf Extract, Chamomilla Recutita (Matricaria) Flower Extract, Echinacea Angustifolia (Coneflower) Extract, Ilex Paraguariensis (Yerba Mater) Leaf Extract, Avena Sativa (Oat) Kernel Extract, Cucumis Sativus (Cucumber) Fruit Extract, Sorbitol, Lecithin, Xanthan Gum, Oleic Acid, Iron Oxides (CI 77491), Phenoxyethanol, Ethylhexylglycerin, Steareth-20, Sodium Chloride, Colloidal Oatmeal, 4-t-Butylcyclohexanol, Pentylene Glycol, Benzalkonium Chloride, Mentha Piperita (Peppermint) Oil, Ceramide NP.